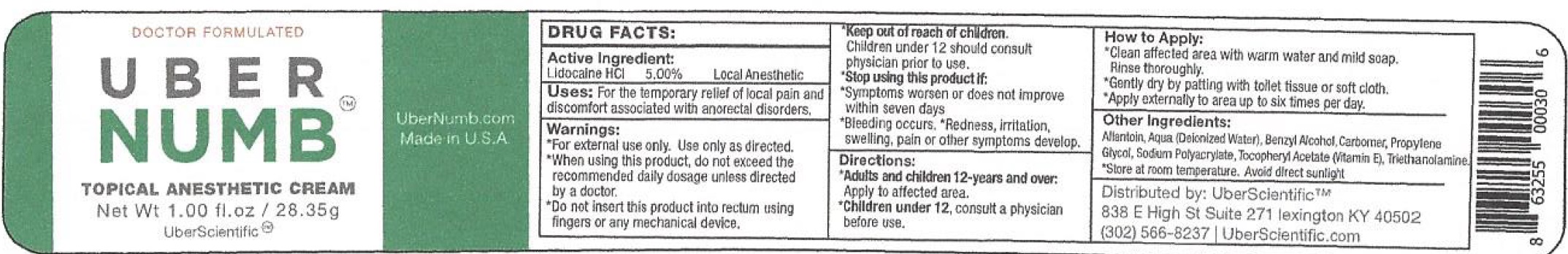 DRUG LABEL: Uber Numb Topical Anesthetic
NDC: 71131-774 | Form: CREAM
Manufacturer: UberScientific, LLC
Category: otc | Type: HUMAN OTC DRUG LABEL
Date: 20231110

ACTIVE INGREDIENTS: LIDOCAINE HYDROCHLORIDE 50 mg/1 g
INACTIVE INGREDIENTS: ALLANTOIN; WATER; BENZYL ALCOHOL; CARBOXYPOLYMETHYLENE; PROPYLENE GLYCOL; .ALPHA.-TOCOPHEROL ACETATE; TROLAMINE

Uber Numb Topical Anesthetic Cream

Active Ingredient:

Lidocaine HCl 5.00%

PURPOSE

Local Anesthetic

Uses:

For the temporary relief of local pain and discomfort associated with anorectal disorders.

Warnings:

- For external use only. Use only as directed.

When using this product,

do not exceed the recommended daily dosage unless directed by a doctor.

Do not insert

this product into rectum using fingers or any mechanical device.

Keep out of reach of children.

Children under 12 should consult physician prior to use.

Stop using this product if:

- Symptoms worsen or does not improve within seven days
- Bleeding occurs. Redness, irritation, swelling, pain or other symptoms develop.

Directions:

- apply to affected area. Adults and children 12-years and over:
- consult a physician before use. Children under 12,
- How to Apply:
- Clean affected area with warm water nad mild soap. Rinse thoroughly.
- Gently dry by patting with toilet tissue or soft cloth.
- Apply externally to area up to six times per day.

Other Ingredients:

Allantoin, Aqua (Deionized Water), Benzyl Alcohol, Carbomer, Propylene Glycol, Sodium Polyacrylate, Tocopheryl Acetate (Vitamin E), Triethanolamine.

- Store at room temperature. Avoid direct sunlight